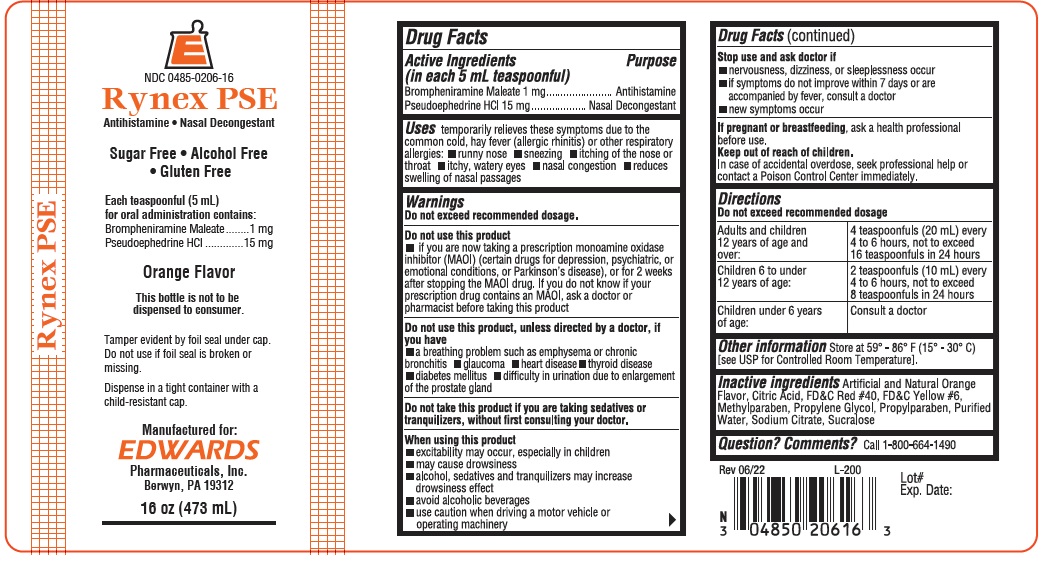 DRUG LABEL: RYNEX PSE
NDC: 0485-0206 | Form: LIQUID
Manufacturer: EDWARDS PHARMACEUTICALS, INC.
Category: otc | Type: HUMAN OTC DRUG LABEL
Date: 20251230

ACTIVE INGREDIENTS: BROMPHENIRAMINE MALEATE 1 mg/5 mL; PSEUDOEPHEDRINE HYDROCHLORIDE 15 mg/5 mL
INACTIVE INGREDIENTS: CITRIC ACID MONOHYDRATE; FD&C RED NO. 40; FD&C YELLOW NO. 6; METHYLPARABEN; PROPYLPARABEN; PROPYLENE GLYCOL; WATER; SODIUM CITRATE, UNSPECIFIED FORM; SUCRALOSE

Ed-RynexPSE 0206

Drug Facts

ACTIVE INGREDIENT

Active Ingredients (in each 5 mL teaspoonful) | Purpose
Brompheniramine Maleate 1 mg | Antihistamine
Pseudoephedrine HCI 15 mg | Decongestant

Uses

temporarily relieves these symptoms due to the common cold, hay fever (allergic rhinitis) or other respiratory allergies:

- runny nose
- sneezing
- itching of the nose or throat
- itchy, watery eyes
- nasal congestion 'reduces swelling of nasal passages

Warnings

On not exceed recommended dosage.

Do not use this product

- if you are now taking a prescription monoamine oxidase inhibitor (MA0I) (certain drugs for depression, psychiatric, or emotional conditions, or Parkinson's disease), or for 2 weeks after stopping the MA0I drug. If you do not know if your prescription drug contains an MA0I, ask a doctor or pharmacist before taking this product

Do not use this product, unless directed by a doctor, if you have

- a breathing problem such as emphysema or chronic bronchitis
- glaucoma
- heart disease
- thyroid disease
- diabetes mellitus
- difficulty in urination due to enlargement of the prostate gland

DO NOT USE

Do not lake this product if you are taking sedatives or tranquilizers, without first consulting your doctor.

When using this product

- excitability may occur, especially in children
- may cause drowsiness
- alcohol, sedatives and tranquilizers may increase drowsiness effect
- avoid alcoholic beverages
- use caution when driving a motor vehicle or operating machinery

Stop use and ask doctor If

- nervousness, dizziness, or sleeplessness occur
- If symptoms do not improve within 7 days or are accompanied by fever, consult a doctor
- new symptoms occur

Keep out of reach of children.

In case of accidental overdose, seek professional help or contact a Poison Control Center immediately.

Directions

Do not exceed recommended dosage

Adults and children 12 years of age and over: | 4teaspoonfuls (20 mL) every 4 to 6 hours, not to exceed 16 teaspoonfuls in 24 hours
Children 6 to under 12 years of age: | 2 teaspoonfuls (10 mL) every 4 to 6 hours, not to exceed 8 teaspoonfuls in 24 hours
Children under 6 years of age | Consult a doctor

Other information

Store at 59° - 86° F (15° - 30 C) [see USP for Controlled Room Temperature]

Inactive ingredients

Artificial and natural orange flavor, Citric Acid, FD&C Red #40, FD&C Yellow #6, Methyl Paraben, Propylene Glycol, Propyl Paraben, Purified Water, Sodium citrate Sucralose

Question? Comments?

Call 1-800-543-9560

PRINCIPAL DISPLAY PANEL - 473 mL Bottle Label

NDC 00485-0206-16

Rynex PSE

Antihistamine • Decongestant

Sugar Free • Alcohol Free •
Gluten Free

Each teaspoonful (5 mL)
for oral administration contains:
Brompheniramine Maleate 1 mg
Pseudoephedrine HCI 15 mg

Orange Flavor
FOR PROFESSIONAL USE ONLY

This bottle is not to be
dispensed to consumer.

Tamper evident by foil seal under cap.
Do not used foil seal is broken or missing.

Dispense in a tight container with a child-
resistant cap.

Manufactured for:
EDWARDS
Pharmaceuticals, Inc.
Ripley, MS 38663
16oz. (473 mL)